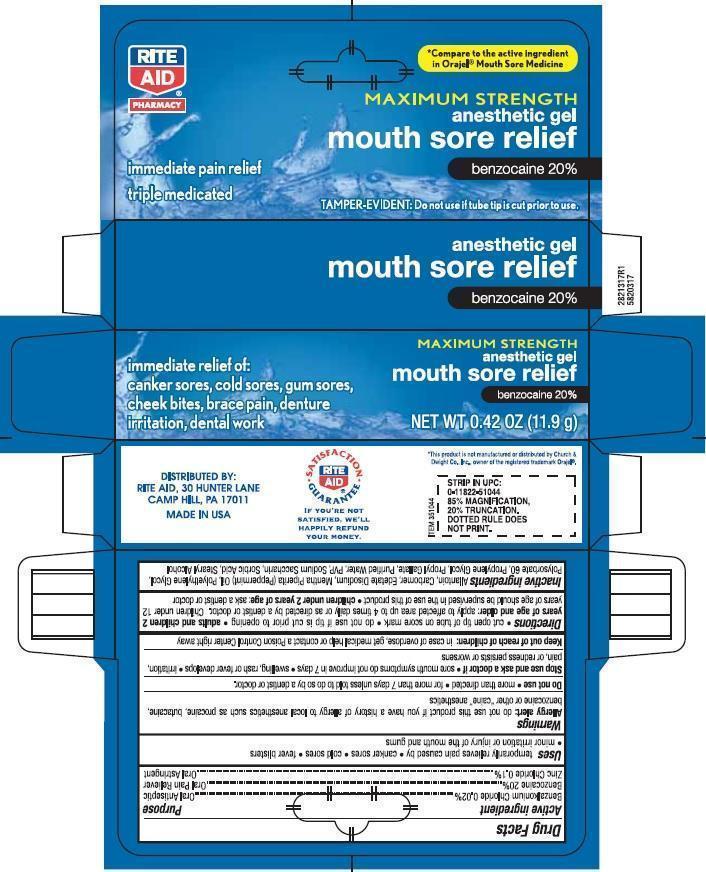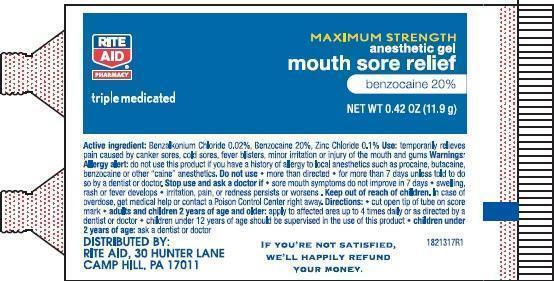 DRUG LABEL: Rite Aid
NDC: 11822-0317 | Form: GEL, DENTIFRICE
Manufacturer: Rite Aid
Category: otc | Type: HUMAN OTC DRUG LABEL
Date: 20130109

ACTIVE INGREDIENTS: BENZOCAINE 20.0 g/100 g; BENZALKONIUM CHLORIDE 0.04 g/100 g; ZINC CHLORIDE 0.1 g/100 g
INACTIVE INGREDIENTS: WATER; POLYETHYLENE GLYCOLS; SACCHARIN SODIUM; SORBIC ACID; POLYSORBATE 60; POVIDONE K90; CARBOMER HOMOPOLYMER TYPE B (ALLYL PENTAERYTHRITOL CROSSLINKED); STEARYL ALCOHOL; EDETATE DISODIUM; ALLANTOIN; PROPYLENE GLYCOL; PROPYL GALLATE; PEPPERMINT OIL

Drug Facts

Active ingredient

Benzalkonium Chloride 0.02% .................................................... Oral Antiseptic

Benzocaine 7.5% ...................................................................... Oral Pain Reliever

Zinc Chloride 0.1% ................................................................... Oral Astringent

Uses

temporarily relieves pain caused by canker sores, cold sores, fever blisters, minor irritation or injury of the mouth and gums

Allergy alert: do not use this product if you have a history of allergy to local anesthetics such as
procaine, butacaine, benzocaine or other “caine” anesthetics

- Do not use more than directed for more than 7 days unless told to do so by a dentist or doctor.
- Stop use and ask a doctor if sore mouth symptoms do not get better in 7 days. swelling, rash or fever develops, irritation, pain or redness persists or worsens

Keep out of reach of children. In case of overdose, get medical help or contact a Poison Control Center right away.

Directions

cut open tip of tube on score mark. do not use if tip is cut prior to opening

Adults and children 2 years of age and older: apply to affected area up to 4 times daily or as directed by a doctor. Children under 12 years should be supervised in the use of this product.

Childern under 2 years of age: ask a dentist or doctor

DOSAGE AND ADMINISTRATION

Adults and children 2 years of age and older: apply to affected area up to 4 times daily or as directed by a doctor. Children under 12 years should be supervised in the use of this product.

Childern under 2 years of age: ask a dentist or doctor

Other Information

Do not use if tip is cut prior to opening.

Inactive ingredients

Allantoin, Carbomer, Edetate Disodium, Mentha Piperota (Peppermint) Oil, Polyethylene Glycol, Polysorbate 60, Propylene Glycol, Propyl Gallate, Purified Water, PVP, Sodium Saccharin, Sorbic Acid, Stearyl Alcohol

PACKAGE LABEL

mm1.jpg

mm2.jpg